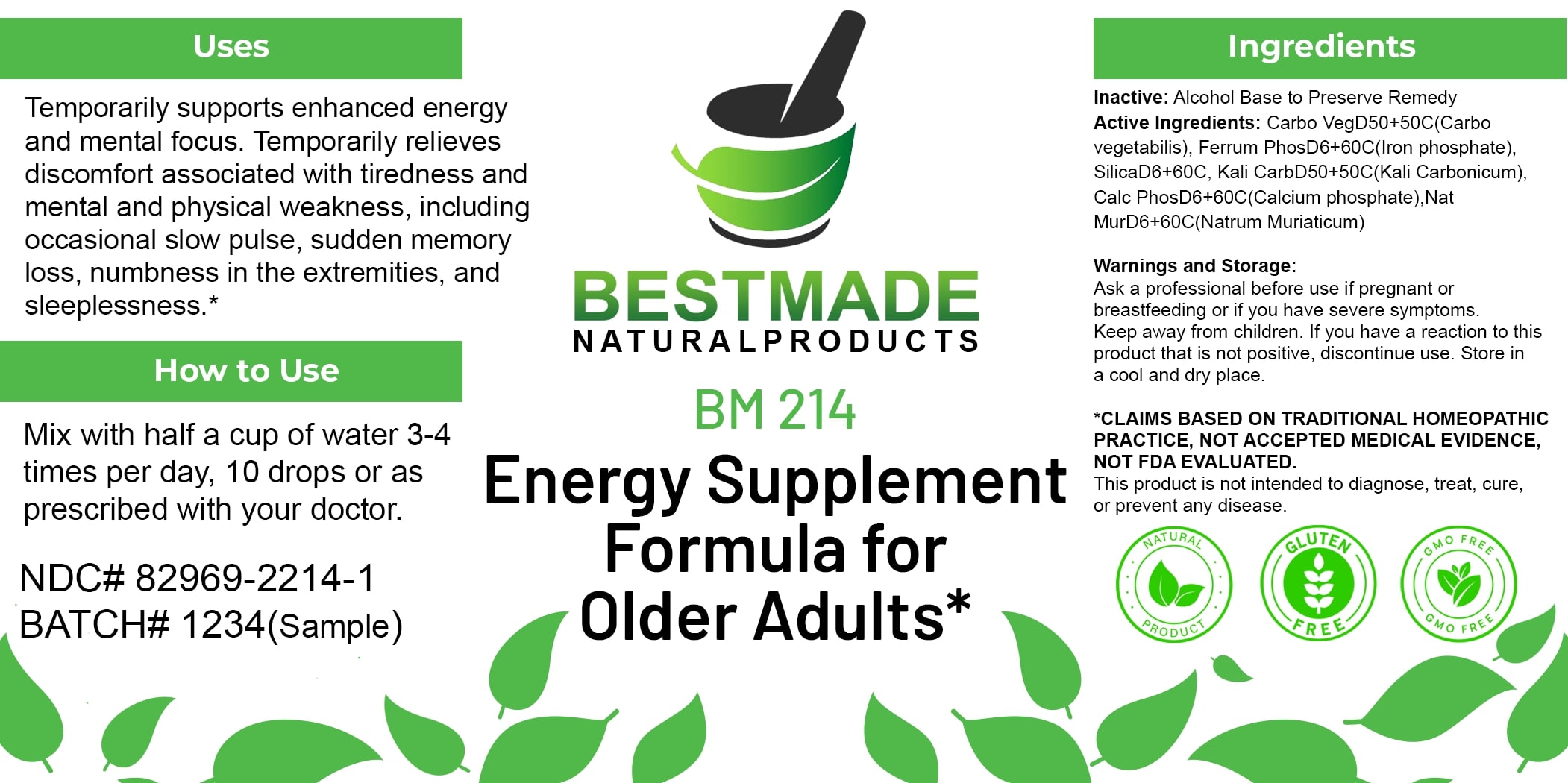 DRUG LABEL: Bestmade Natural Products BM214
NDC: 82969-2214 | Form: LIQUID
Manufacturer: Bestmade Natural Products
Category: homeopathic | Type: HUMAN OTC DRUG LABEL
Date: 20250303

ACTIVE INGREDIENTS: FERROSOFERRIC PHOSPHATE 30 [hp_C]/30 [hp_C]; TRIBASIC CALCIUM PHOSPHATE 30 [hp_C]/30 [hp_C]; ACTIVATED CHARCOAL 30 [hp_C]/30 [hp_C]; SODIUM CHLORIDE 30 [hp_C]/30 [hp_C]; SILICA 30 [hp_C]/30 [hp_C]; POTASSIUM CARBONATE 30 [hp_C]/30 [hp_C]
INACTIVE INGREDIENTS: ALCOHOL 30 [hp_C]/30 [hp_C]

BM214

DOSAGE AND ADMINISTRATION

How to Use

Mix with half a cup of water 3-4 times per day, 10 drops or as prescribed with your doctor.

Uses

Temporarily supports enhanced energy and mental focus. Temporarily relieves discomfort associated with tiredness and mental and physical weakness, including occasional slow pulse, sudden memory loss, numbness in the extremities, and sleeplessness.*

*CLAIMS BASED ON TRADITIONAL HOMEOPATHIC PRACTICE, NOT ACCEPTED MEDICAL EVIDENCE. NOT FDA EVALUATED.

This product is not intended to diagnose, treat, cure, or prevent any disease.

INACTIVE INGREDIENT

Ingredients

Inactive: Alcohol Base to Preserve Remedy

ACTIVE INGREDIENT

Active Ingredients: Carbo VegD50+50C(Carbo Vegetabilis), Ferrum PhosD6+60C(Iron phosphate), SilicaD6+60C, Kali CarbD50+50C(Kali Carbonicum), Calc PhosD6+60C(Calcium phosphate), Nat MurD6+60C(Natrum Muriaticum)

KEEP OUT OF REACH OF CHILDREN

Warnings and Storage:

Ask a professional before use if pregnant or breastfeeding or if you have severe symptoms. Keep away from children. If you have a reaction to this product that is not positive, discontinue use. Store in a cool and dry place.

Warnings and Storage:

Ask a professional before use if pregnant or breastfeeding or if you have severe symptoms. Keep away from children. If you have a reaction to this product that is not positive, discontinue use. Store in a cool and dry place.

*CLAIMS BASED ON TRADITIONAL HOMEOPATHIC PRACTICE, NOT ACCEPTED MEDICAL EVIDENCE. NOT FDA EVALUATED.

This product is not intended to diagnose, treat, cure, or prevent any disease.

Uses

Temporarily supports enhanced energy and mental focus. Temporarily relieves discomfort associated with tiredness and mental and physical weakness, including occasional slow pulse, sudden memory loss, numbness in the extremities, and sleeplessness.*

*CLAIMS BASED ON TRADITIONAL HOMEOPATHIC PRACTICE, NOT ACCEPTED MEDICAL EVIDENCE. NOT FDA EVALUATED.

This product is not intended to diagnose, treat, cure, or prevent any disease.

Entire package label